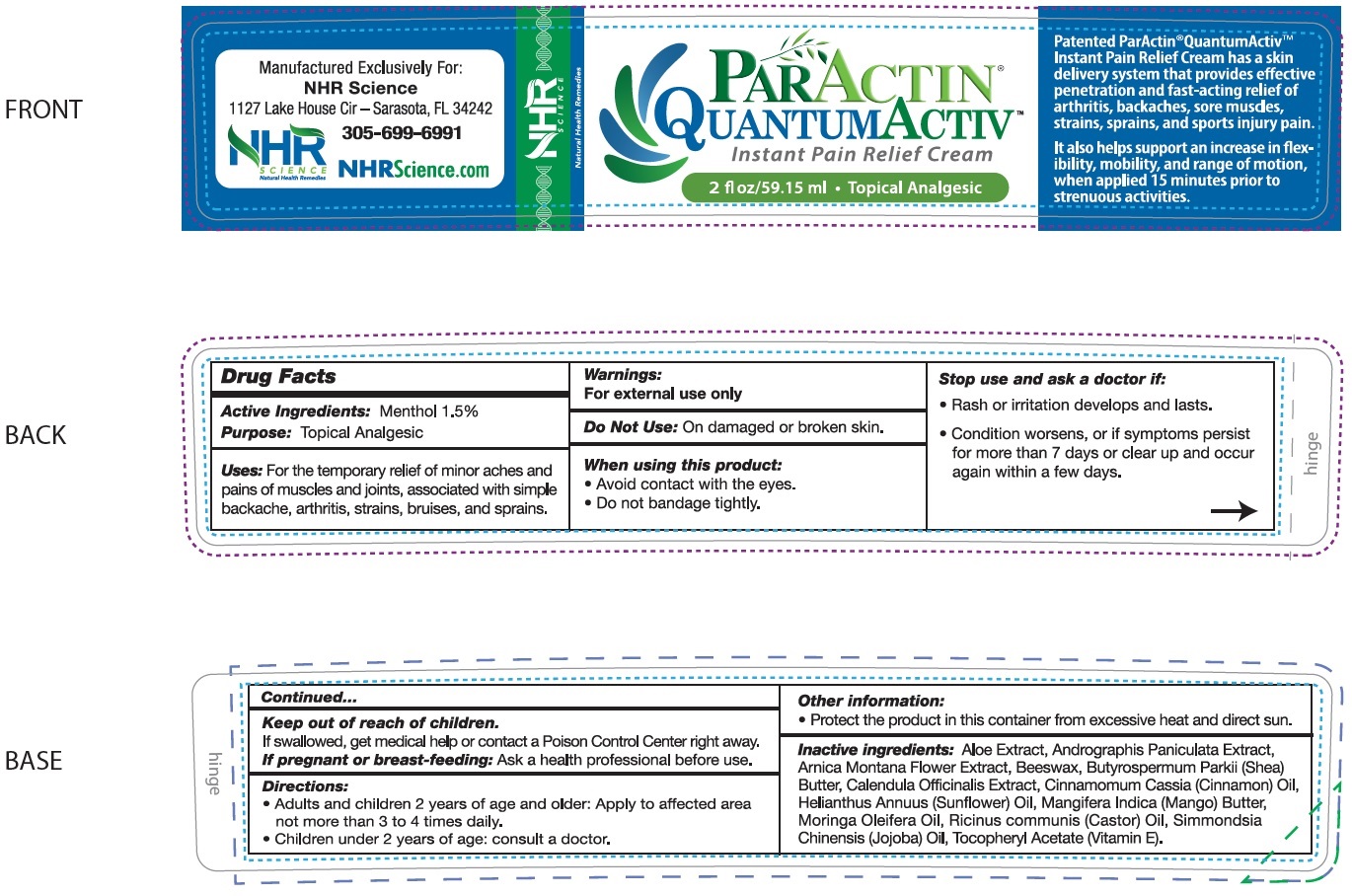 DRUG LABEL: PARACTIN QuantumActiv Pain Relief Cream
NDC: 83224-372 | Form: CREAM
Manufacturer: NHR SCIENCE CORP
Category: otc | Type: HUMAN OTC DRUG LABEL
Date: 20231106

ACTIVE INGREDIENTS: MENTHOL 15 mg/1 mL
INACTIVE INGREDIENTS: ALOE; ANDROGRAPHIS PANICULATA WHOLE; ARNICA MONTANA FLOWER; YELLOW WAX; SHEA BUTTER; CALENDULA OFFICINALIS FLOWER; CHINESE CINNAMON OIL; HELIANTHUS ANNUUS FLOWERING TOP; MANGO; CASTOR OIL; JOJOBA OIL; .ALPHA.-TOCOPHEROL ACETATE

PARACTIN QuantumActiv Pain Relief Cream

Active Ingredients:

Menthol 1.5%

Purpose:

Topical Analgesic

Uses:

For the temporary relief of minor aches and pains of muscles and joints, associated with simple backache, arthritis, strains, bruises, and sprains.

Warnings:

For external use only

Do Not Use:

On damaged or broken skin.

When using this product:

- Avoid contact with the eyes.
- Do not bandage tightly.

Stop use and ask a doctor if:

- Rash or irritation develops and lasts.
- Condition worsens or if symptoms persist for more than 7 days or clear up and occur again within a few days.

Keep out of reach of children.

If swallowed, get medical help or contact a Poison Control Center right away.

If pregnant or breast-feeding:

Ask a health professional before use.

Directions:

- Adults and children 2 years of age and older: Apply to affected area not more than 3 to 4 times daily.
- Children under 2 years of age: consult a doctor.

Other information:

- Protect the product in this container from excessive heat and direct sun.

Inactive ingredients:

Aloe Extract, Andrographis Paniculata Extract, Arnica Montana Flower Extract, Beeswax, Butyrospermum Parkii (Shea) Butter, Calendula Officinalis Extract, Cinnamomum Cassia (Cinnamon) Oil, Helianthus Annuus (Sunflower) Oil, Mangifera Indica (Mango) Butter, Moringa Oleifera Oil, Ricinus communis (Castor) Oil, Simmondsia Chinensis (Jojoba) Oil, Tocopheryl Acetate (Vitamin E).